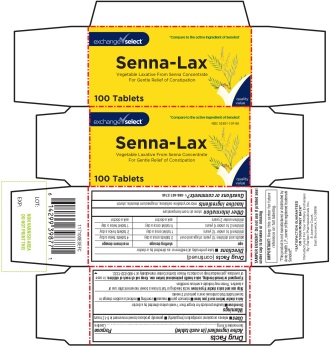 DRUG LABEL: Exchange select
NDC: 55301-107 | Form: TABLET
Manufacturer: ARMY AND AIR FORCE EXCHANGE SERVICE
Category: otc | Type: HUMAN OTC DRUG LABEL
Date: 20250911

ACTIVE INGREDIENTS: SENNOSIDES 8.6 mg/1 1
INACTIVE INGREDIENTS: MICROCRYSTALLINE CELLULOSE; MAGNESIUM STEARATE; STARCH, CORN

Exchange select senna-Lax

Drug Facts
Active ingredient (in each tablet)

Sennosides 8.6 mg

Purpose

Laxative

Uses

- relieves occasional constipation (irregularity)
- generally produces a bowel movement in 6–12 hours

Warnings

Do not use

- laxative products for longer than 1 week unless directed by a doctor

Ask a doctor before use if you have

- stomach pain
- nausea
- vomiting
- noticed a sudden change in bowel habits that continues over a period of 2 weeks

Stop use and ask a doctor ifyou haverectal bleeding or fail to have a bowel movement after use of a laxative. These may indicate a serious condition.

PREGNANCY OR BREAST FEEDING

If pregnant or breast-feeding, ask a health professional before use.

Keep out of reach of children.In case of overdose, get medical help or contact a Poison Control Center immediately at 1-800-22-1222.

Directions

- take preferably at bedtime or as directed by a doctor

age | starting dosage | maximum dosage
adults and children 12 years of age and over | 2 tablets once a day | 4 tablets twice a day
children 6 to under 12 years | 1 tablet once a day | 2 tablets twice a day
children 2 to under 6 years | 1/2 tablet once a day | 1 tablet twice a day
children under 2 years | ask a doctor | ask a doctor

Other Information

- store at room temperature

Inactive ingredients

microcrystalline cellulose, magnesium stearate, starch

Questions or comments?

1-866-467-2748

TAMPER EVIDENT: Do not use if printed seal under cap is broken or missing

IMPORTANT: Keep this carton for future reference on full labeling.

*This product is not manufactured or distributed by Avrio Health L.P., owner of the registered trademark Senokot®

“ SATISFACTION GUARANTEED OR YOUR MONEY BACK”
Manufactured For Your Military Exchanges By: Raritan Pharmaceuticals Inc., 8 Joanna Court, East Brunswick, NJ 08816

PACKAGE LABEL

*Compare to the active ingredient of Senokot®

exchange√select

Senna-Lax

Vegetable Laxative From Senna Concentrate For Gentle Relief of Constipation

100 Tablets

*Compare to the active ingredient of Senokot®

NDC 55301-107-00

exchange√select

Senna-Lax

Vegetable Laxative From Senna Concentrate For Gentle Relief of Constipation

100 Tablets